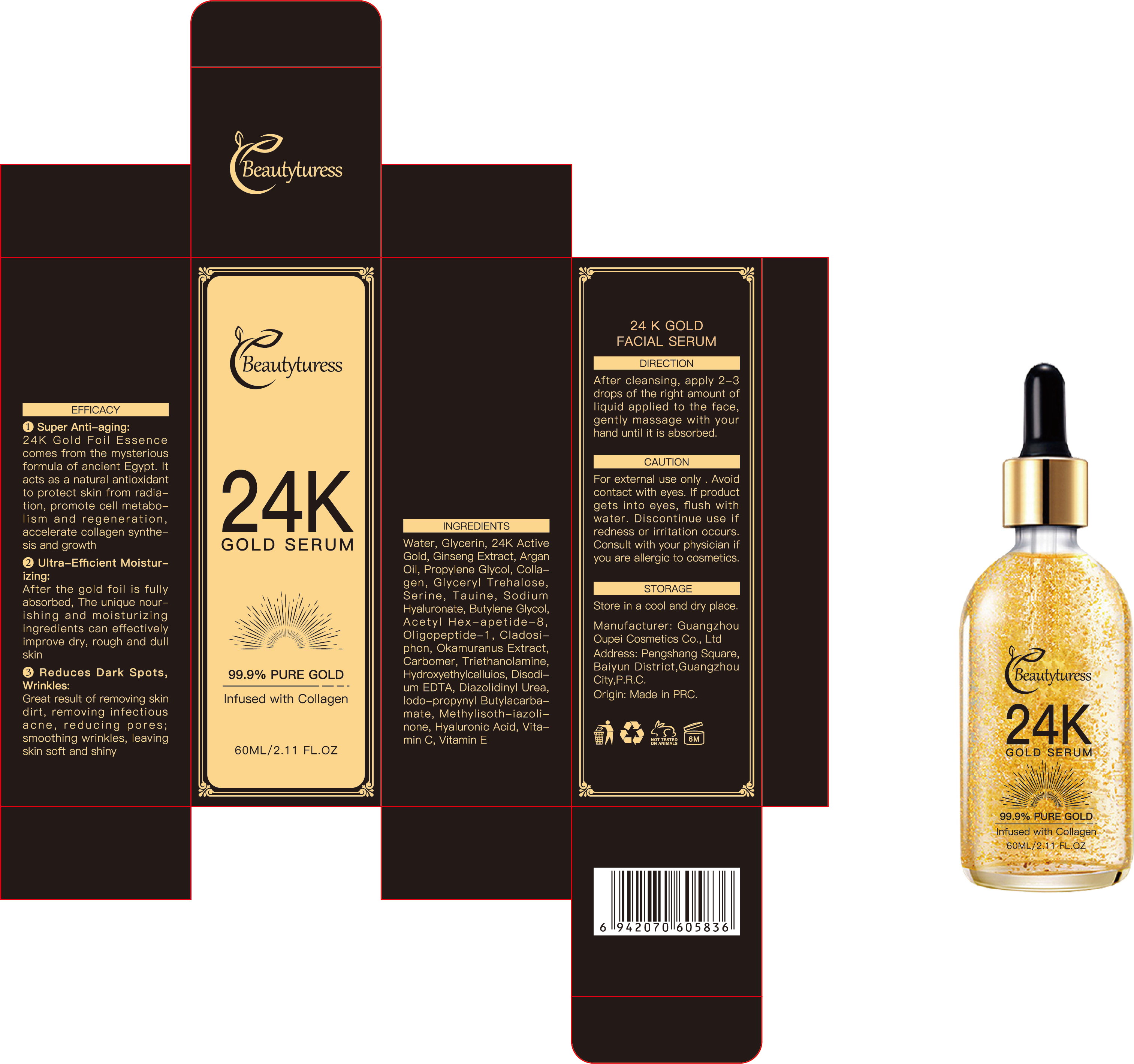 DRUG LABEL: Beautyturess 24k Gold Essence
NDC: 84753-010 | Form: EMULSION
Manufacturer: Guangdong Bisutang Biotechnology Co., Ltd.
Category: otc | Type: HUMAN OTC DRUG LABEL
Date: 20241015

ACTIVE INGREDIENTS: DIGLYCERIN 0.129 g/60 mL; NIACINAMIDE 0.072 g/60 mL
INACTIVE INGREDIENTS: GLYCERYL ACRYLATE/ACRYLIC ACID COPOLYMER (300000 CP AT 2%); 1,2-HEXANEDIOL; BETAINE; TREHALOSE; CUPRIC TRIETHANOLAMINE; CETYL HYDROXYETHYLCELLULOSE (350000 MW); METHYLPARABEN; WATER; METHYLISOTHIAZOLINONE; HYDROGENATED CASTOR OIL

ACTIVE INGREDIENT

GLYCERIN

NIACINAMIDE

PURPOSE

After cleansing andtoning, take an appropriate amount ofthis product and apply it evenly on theface, massage until absorbed

Ask Doctor

If you have a history of skin allergies or have sensitive skin, it is advisable to consult a doctor before using this product.

DOSAGE AND ADMINISTRATION

Apply once daily to clean face and neck, avoiding the eye area

WHEN USING

Avoid contact with eyes and broken skin. If redness, swelling, or irritation occurs, discontinue use immediately and seek medical advice.

WARNINGS

Risk InformationFor external use only
Mention de risquesPour usage externe seulement
Do not use on damaged or broken skin.
Ne pas utiliser sur la peau endommagée ou avec des lésions
If rash occurs, discontinue use and consult a health care practitioner.
En présence d'une éruption cutanée, cesser l'utilisation et consulter un praticien de soins de santé
When using this product keep out of eyes. Rinse with water to remove.
Eviter tout contact avec les yeux. Rincer a l'eau le cas échéant
Keep out of reach of children. If swallowed, get medical help or contact a Poison Control Center right away.
Tenir hors de portée des enfants
En cas d'ingestion, consulter un médecin ou appeler un centre antipoison immédiatement.

INDICATIONS AND USAGE

Temporarily protects and helps relieve dry or cracked skin
Beneficlal for face, hands, body, and legs

Keep out of reach of children. If swallowed, get medical help or contact a Poison Control Center right away.
Tenir hors de portée des enfants
En cas d'ingestion, consulter un médecin ou appeler un centre antipoison immédiatement.

INACTIVE INGREDIENT

AQUA
GLYCERIN
AQUA
GLYCERIN
GLYCERYL ACRYLATE/ACRYLIC ACID COPOLYMER
1,2-HEXANEDIOL
PVM/MA COPOLYMER
BETAINE
TREHALOSE
PROPYLENE GLYCOL
DIAZOLIDINYL UREA
IODOPROPYNYL BUTYLCARBAMATE
ACRYLATES/C10-30 ALKYL ACRYLATE CROSSPOLYMER
TRIETHANOLAMINE
METHYLPARABEN
NIACINAMIDE
HYDROXYETHYLCELLULOSE
DISODIUM EDTA
AQUA
GLYCERIN
BETAINE
TAURINE
SERINE
SODIUM HYALURONATE
1,2-HEXANEDIOL
HYDROXYACETOPHENONE
PEG-40 HYDROGENATED CASTOR OIL
FRAGRANCE
AQUA
CAPRYLYL GLYCOL
ACETYL HEXAPEPTIDE-8
AQUA
BUTYLENE GLYCOL
1,2-HEXANEDIOL
HYDROXYACETOPHENONE
ACETYL TETRAPEPTIDE-5
AQUA
GLYCERIN
METHYLPARABEN
PROPYLPARABEN
OLIGOPEPTIDE-1
GOLD
AQUA
CLADOSIPHON OKAMURANUS EXTRACT
PROPYLENE GLYCOL
DIAZOLIDINYL UREA
IODOPROPYNYL BUTYLCARBAMATE
AQUA
BUTYLENE GLYCOL
ALOE BARBADENSIS LEAF EXTRACT
PHENOXYETHANOL